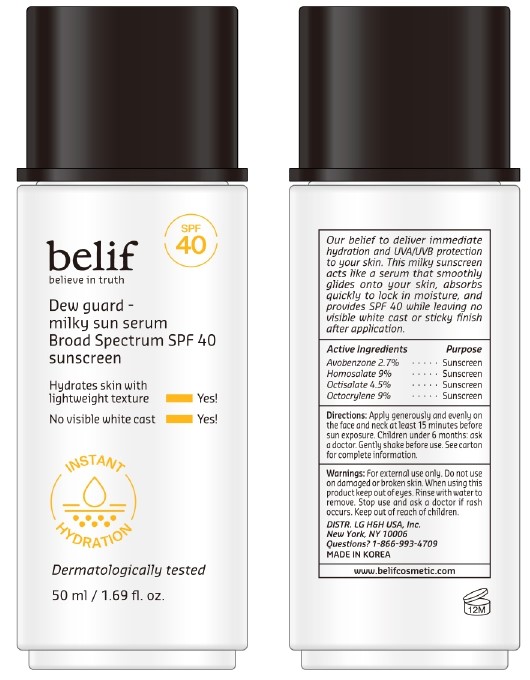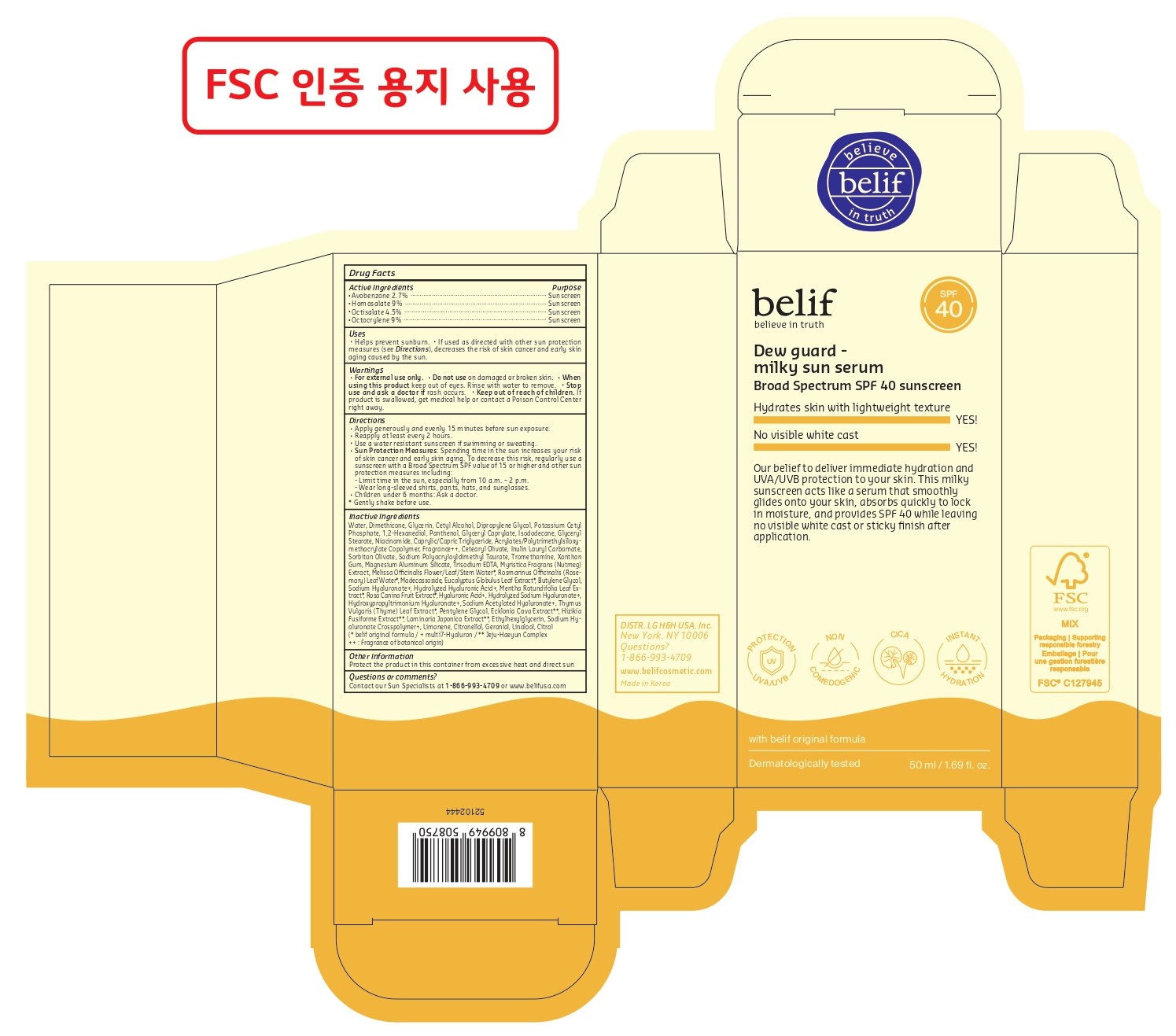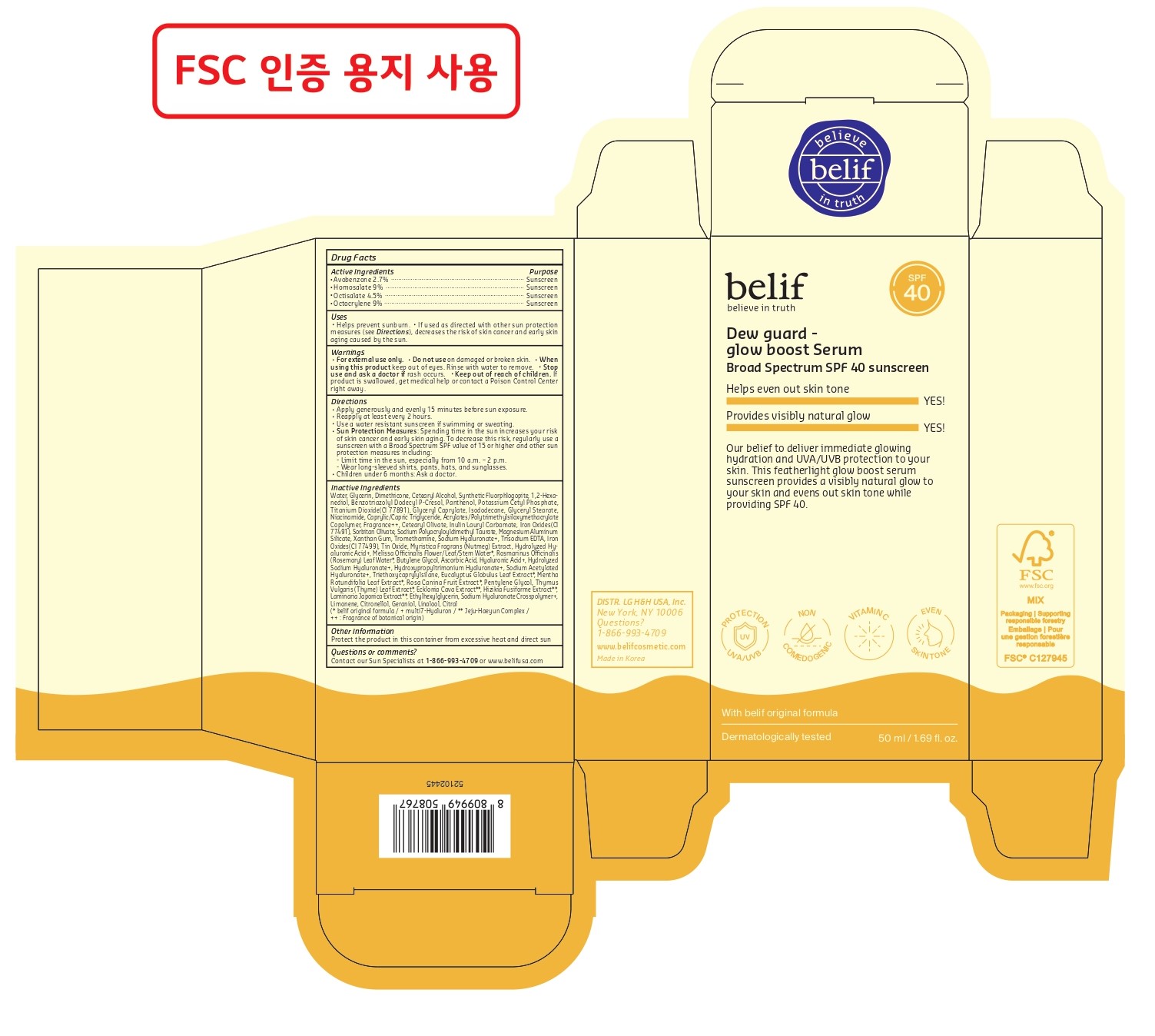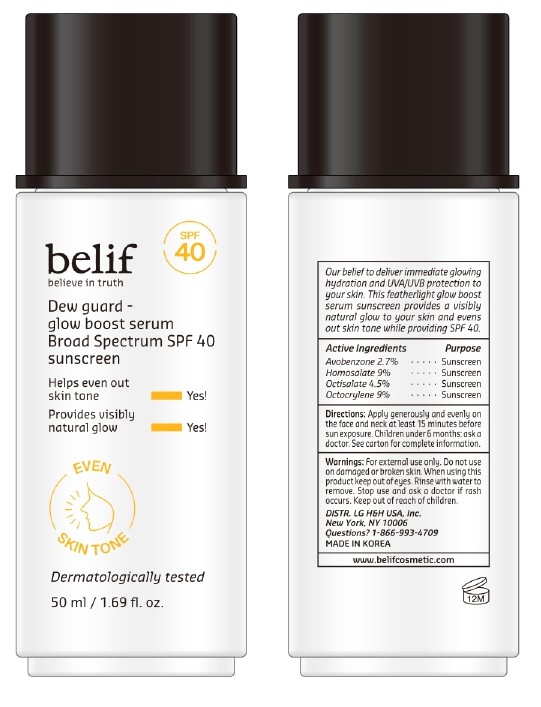 DRUG LABEL: belif Dew guard - milky sun serum Broad Spectrum SPF 40 sunscreen
NDC: 53208-741 | Form: CREAM
Manufacturer: LG H&H CO., LTD.
Category: otc | Type: HUMAN OTC DRUG LABEL
Date: 20250317

ACTIVE INGREDIENTS: HOMOSALATE 9 g/100 g; AVOBENZONE 2.7 g/100 g; OCTISALATE 4.5 g/100 g; OCTOCRYLENE 9 g/100 g
INACTIVE INGREDIENTS: CITRAL; XANTHAN GUM; MELISSA OFFICINALIS FLOWERING TOP; SODIUM HYALURONATE; DIMETHICONE; CETYL ALCOHOL; ISODODECANE; WATER; GLYCERYL CAPRYLATE; PANTHENOL; CAPRYLIC/CAPRIC TRIGLYCERIDE; SORBITAN OLIVATE; MADECASSOSIDE; LIMONENE, (+)-; GERANIOL; MENTHA X ROTUNDIFOLIA LEAF; BUTYLENE GLYCOL; SODIUM ACETYLATED HYALURONATE; PENTYLENE GLYCOL; ETHYLHEXYLGLYCERIN; TROMETHAMINE; THYMUS VULGARIS (THYME) LEAF; POTASSIUM CETYL PHOSPHATE; CETEARYL OLIVATE; INULIN LAURYL CARBAMATE; NUTMEG; ECKLONIA CAVA; LAMINARIA JAPONICA; LINALOOL; DIPROPYLENE GLYCOL; NIACINAMIDE; ROSEMARY OIL; ROSA CANINA FRUIT; SODIUM POLYACRYLOYLDIMETHYL TAURATE; TRISODIUM EDTA; SARGASSUM FUSIFORME; 1,2-HEXANEDIOL; CITRONELLOL; GLYCERYL STEARATE; MAGNESIUM ALUMINUM SILICATE; EUCALYPTUS GLOBULUS LEAF; HYALURONIC ACID

Active Ingredients

Avobenzone 2.7%

Homosalate 9%

Octisalate 4.5%

Octocrylene 9%

Purpose

Sunscreen

Uses

- Helps prevent sunburn.
- If used as directed with other sun protection measures (see Directions), decreases the risk of skin cancer and early skin aging caused by the sun.

WARNINGS

For external use only.

Do not use on damaged or broken skin.

When using this product keep out of eyes. Rinse with water to remove.

Stop use and ask a doctor if rash occurs.

Keep out of reach of children.

DOSAGE AND ADMINISTRATION

If product is swallowed, get medical help or contact a Poison Control Center right away.

Directions

- Apply generously and evenly 15 minutes before sun exposure.
- Reapply at least every 2 hours.
- Use a water resistant sunscreen if swimming or sweating.
- Sun Protection Measures: Spending time in the sun increases your risk of skin cancer and early skin aging. To decrease this risk, regularly use a sunscreen with a Broad Spectrum SPF value of 15 or higher and other sun protection measures including:
  - Limit time in the sun, especially from 10 a.m. – 2 p.m.
  - Wear long-sleeved shirts, pants, hats, and sunglasses.
- Children under 6 months: Ask a doctor.
- Gently shake before use.

Inactive Ingredients

Belif Dew Guard-milky sun serum: Water, Dimethicone, Glycerin, Cetyl Alcohol, Dipropylene Glycol, Potassium Cetyl Phosphate, 1,2-Hexanediol, Panthenol, Glyceryl Caprylate, Isododecane, Glyceryl Stearate, Niacinamide, Caprylic/Capric Triglyceride, Acrylates/Polytrimethylsiloxymethacrylate Copolymer, Fragrance++, Cetearyl Olivate, Inulin Lauryl Carbamate, Sorbitan Olivate, Sodium Polyacryloyldimethyl Taurate, Tromethamine, Xanthan Gum, Magnesium Aluminum Silicate, Trisodium EDTA, Myristica Fragrans (Nutmeg) Extract, Melissa Offcinalis Flower/Leaf/Stem Water*, Rosmarinus Offcinalis (Rosemary) Leaf Water*, Madecassoside, Eucalyptus Globulus Leaf Extract*, Butylene Glycol, Sodium Hyaluronate+, Hydrolyzed Hyaluronic Acid+, Mentha Rotundifolia Leaf Extract*, Rosa Canina Fruit Extract*, Hyaluronic Acid+, Hydrolyzed Sodium Hyaluronate+, Hydroxypropyltrimonium Hyaluronate+, Sodium Acetylated Hyaluronate+, Thymus Vulgaris (Thyme) Leaf Extract*, Pentylene Glycol, Ecklonia Cava Extract**, Hizikia Fusiforme Extract**, Laminaria Japonica Extract**, Ethylhexylglycerin, Sodium Hyaluronate Crosspolymer+, Limonene, Citronellol, Geraniol, Linalool, Citral

(* belif original formula / + multi7-Hyaluron / ** Jeju-Haeyun Complex / ++ : Fragrance of botanical origin)

Belif Dew Guard-glow boost Serum: Water, Glycerin, Dimethicone, Cetearyl Alcohol, Synthetic Fluorphlogopite, 1,2-Hexanediol, Benzotriazolyl Dodecyl P-Cresol, Panthenol, Potassium Cetyl Phosphate, Titanium Dioxide(CI 77891), Glyceryl Caprylate, Isododecane, Glyceryl Stearate, Niacinamide, Caprylic/Capric Triglyceride, Acrylates/Polytrimethylsiloxymethacrylate Copolymer, Fragrance++, Cetearyl Olivate, Inulin Lauryl Carbamate, Iron Oxides(CI 77491), Sorbitan Olivate, Sodium Polyacryloyldimethyl Taurate, Magnesium Aluminum Silicate, Xanthan Gum, Tromethamine, Sodium Hyaluronate+, Trisodium EDTA, Iron Oxides(CI 77499), Tin Oxide, Myristica Fragrans (Nutmeg) Extract, Hydrolyzed Hyaluronic Acid+, Melissa Offcinalis Flower/Leaf/Stem Water*, Rosmarinus Offcinalis
(Rosemary) Leaf Water*, Butylene Glycol, Ascorbic Acid, Hyaluronic Acid+, Hydrolyzed Sodium Hyaluronate+, Hydroxypropyltrimonium Hyaluronate+, Sodium Acetylated Hyaluronate+, Triethoxycaprylylsilane, Eucalyptus Globulus Leaf Extract*, Mentha Rotundifolia Leaf Extract*, Rosa Canina Fruit Extract*, Pentylene Glycol, Thymus Vulgaris (Thyme) Leaf Extract*, Ecklonia Cava Extract**, Hizikia Fusiforme Extract**, Laminaria Japonica Extract**, Ethylhexylglycerin, Sodium Hyaluronate Crosspolymer+, Limonene, Citronellol, Geraniol, Linalool, Citral

(* belif original formula / + multi7-Hyaluron / ** Jeju-Haeyun Complex / ++ : Fragrance of botanical origin)

Other Information

Protect the product in this container from excessive heat and direct sun

Questions or comments?

Contact our Sun Specialists at 1-866-993-4709 or www.belifusa.com